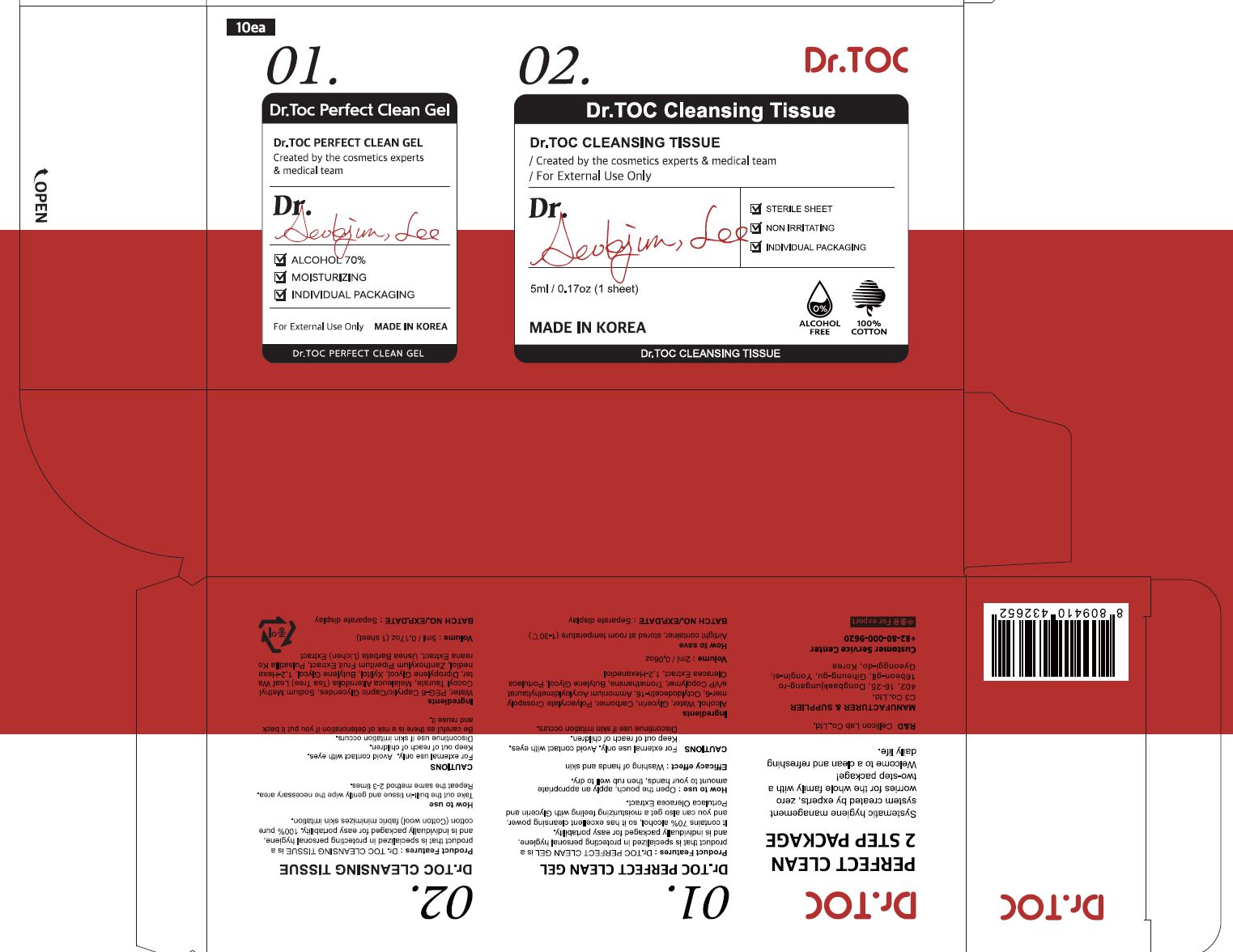 DRUG LABEL: Dr TOC PERFECT CLEAN gel
NDC: 70818-028 | Form: LIQUID
Manufacturer: C3 Co., Ltd.
Category: otc | Type: HUMAN OTC DRUG LABEL
Date: 20210214

ACTIVE INGREDIENTS: ALCOHOL 74 mL/100 mL
INACTIVE INGREDIENTS: WATER

C3 Co., Ltd. - isLeaf Hand Cleaning Gel

ACTIVE INGREDIENT

Alcohol

INACTIVE INGREDIENT

Water, Glycerin, Carbomer, Polyacrylate Crosspolymer-6, Octyldodeceth-16, Ammonium Acryloyldimethyltaurate/VP Copolymer, Tromethamine, Butylene Glycol, Portulaca Oleracea Extract, 1,2-Hexanediol

PURPOSE

Antiseptic

keep out of reach of the children

INDICATIONS AND USAGE

Open the pouch, apply an appropriate amount to your hands, then rub well to dry.

WARNINGS

For external use only.

Avoid contact with eyes.

Keep out of reach of children.

Discontinue use if skin irritation occurs.

DOSAGE AND ADMINISTRATION

for external use only